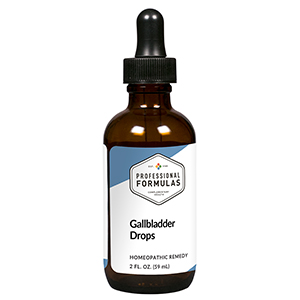 DRUG LABEL: Gallbladder Drops
NDC: 63083-5006 | Form: LIQUID
Manufacturer: Professional Complementary Health Formulas
Category: homeopathic | Type: HUMAN OTC DRUG LABEL
Date: 20190815

ACTIVE INGREDIENTS: MILK THISTLE 2 [hp_X]/59 mL; AMARYLLIS BELLADONNA WHOLE 3 [hp_X]/59 mL; CHELIDONIUM MAJUS WHOLE 3 [hp_X]/59 mL; CHIONANTHUS VIRGINICUS BARK 3 [hp_X]/59 mL; VERONICASTRUM VIRGINICUM WHOLE 3 [hp_X]/59 mL; CHOLESTEROL 4 [hp_X]/59 mL; CITRULLUS COLOCYNTHIS FRUIT PULP 6 [hp_X]/59 mL; BOS TAURUS BILE 6 [hp_X]/59 mL; BOS TAURUS GALLBLADDER 6 [hp_X]/59 mL; BEEF LIVER 6 [hp_X]/59 mL
INACTIVE INGREDIENTS: ALCOHOL; WATER

HGD

ACTIVE INGREDIENTS

Carduus marianus 2X
Belladonna 3X
Chelidonium majus 3X
Chionanthus virginica 3X
Leptandra virginica 3X
Cholesterinum 4X
Colocynthis 6X
Fel tauri 6X
Gallbladder 6X
Liver 6X

QUESTIONS

Professional Formulas

PO Box 2034 Lake Oswego, OR 97035

INDICATIONS

For the temporary relief of mild abdominal pain or cramping, nausea or vomiting, indigestion, itching, or chills.*

PURPOSE

*Claims based on traditional homeopathic practice, not accepted medical evidence. Not FDA evaluated.

WARNINGS

Severe or persistent symptoms may be a sign of a serious condition. Consult a doctor promptly if you are experiencing severe abdominal or chest pain, or if accompanied by a fever. Keep out of the reach of children. In case of overdose, get medical help or contact a poison control center right away. If pregnant or breastfeeding, ask a healthcare professional before use.

Keep out of the reach of children.

PREGNANCY OR BREAST FEEDING

If pregnant or breastfeeding, ask a healthcare professional before use.

DIRECTIONS

Place drops under tongue 30 minutes before/after meals. Adults and children 12 years and over: Take 10 drops up to 3 times per day. Consult a physician for use in children under 12 years of age.

OTHER INFORMATION

Tamper resistant. If seal is broken, do not use. After opening, close container tightly and store at room temperature away from heat.

INACTIVE INGREDIENTS

20% ethanol, purified water.

LABEL

Est 1985

Professional Formulas

Complementary Health

Gallbladder Drops

Homeopathic Remedy

2 FL. OZ. (59 mL)